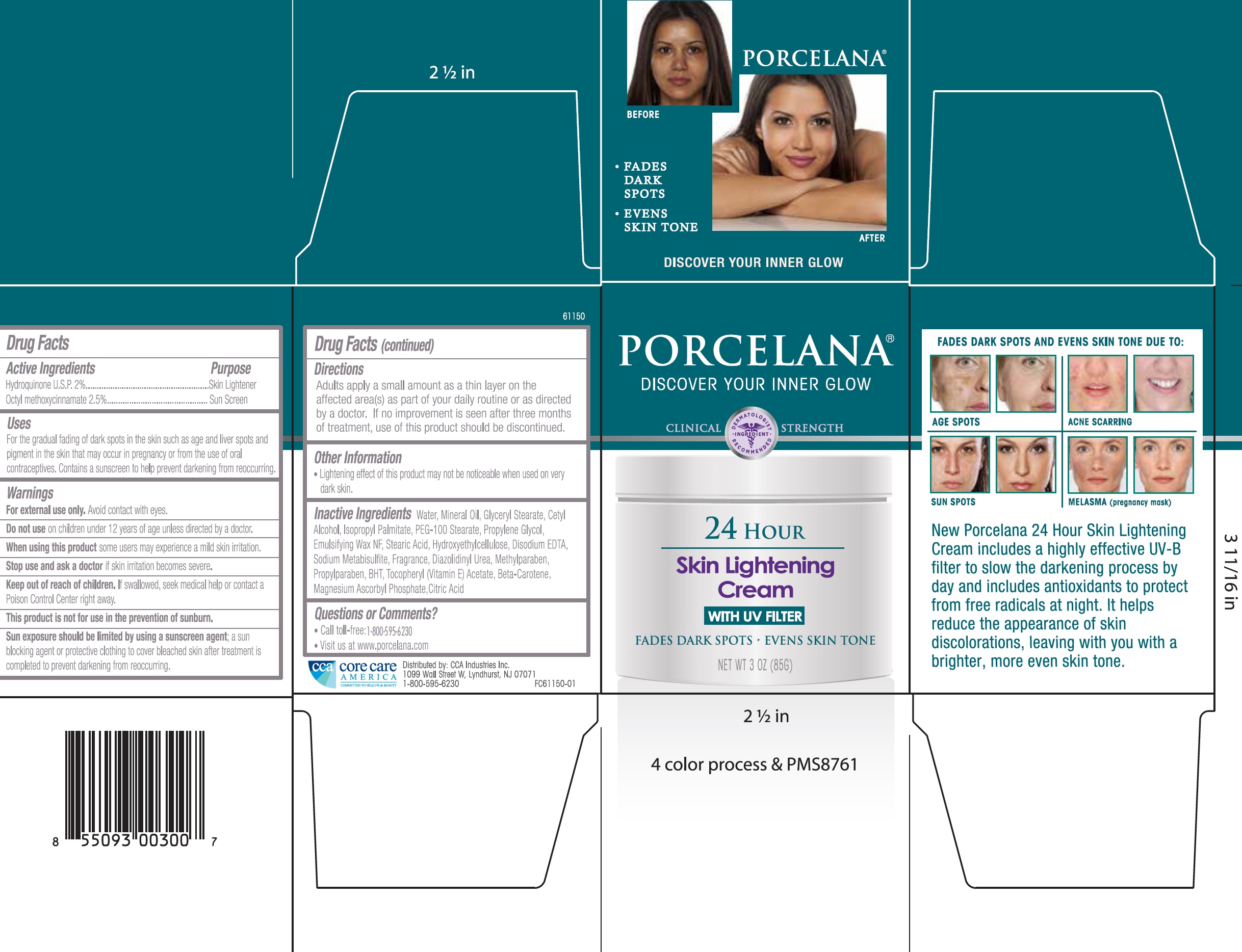 DRUG LABEL: Porcelana 24 Hour Skin Lightening
NDC: 61543-0000 | Form: CREAM
Manufacturer: CCA Industries Inc.
Category: otc | Type: HUMAN OTC DRUG LABEL
Date: 20190409

ACTIVE INGREDIENTS: HYDROQUINONE 20 mg/1 g; OCTINOXATE 25 mg/1 g
INACTIVE INGREDIENTS: WATER; MINERAL OIL; GLYCERYL MONOSTEARATE; CETYL ALCOHOL; ISOPROPYL PALMITATE; PEG-100 STEARATE; PROPYLENE GLYCOL; STEARIC ACID; EDETATE DISODIUM ANHYDROUS; SODIUM METABISULFITE; DIAZOLIDINYL UREA; METHYLPARABEN; PROPYLPARABEN; BUTYLATED HYDROXYTOLUENE; .ALPHA.-TOCOPHEROL; BETA CAROTENE; MAGNESIUM ASCORBYL PHOSPHATE; CITRIC ACID MONOHYDRATE

Porcelana 24 Hour Skin Lightening Cream

Active Ingredient

Hydroquinone U.S.P. 2%

Octyl methoxycinnamate 2.5%

Purpose

Skin Lightener

Sun Screen

Uses:

For the gradual fading of dark spots in the skin such as age liver spots and pigment in the skin that may occur in pregnancy or from the use of oralcontraceptives. Contains a sunscreen to help prevent darkening from reoccurring.

Warnings

For External use only. Avoid contact with eyes.

Do not use

on children under 12 years of age unless directed by a doctor.

When using this product

some users may experience a mild skin irritation.

Stop use and ask a doctor

if skin irritation becomes severe.

Keep out of the reach of children.

If swallowed, seek medical help or contact a Poison Control Center right away.

This product is not for use in the prevention of sunburn,

Sun exposure should be limited by using a sunscreen agent: a sun blocking agent or protective clothing to cover bleached skin after treatment is completed to prevent darkening from reoccurring.

Directions

Adults apply a small amount as a thin layer on the affected area(s) as part of your daily routine or as directed by a doctor. If no improvement is seen after three months of treatment, use of this product should be discontinued.

Other Information

- Lightening effect of this product may not be noticeable when used on very dark skin.

Inactive Ingredients

Water, Mineral Oil, Glyceryl Stearate, Cetyl Alcohol, Isopropyl Palmitate, PEG-100 Stearate, Propylene Glycol, Emulsifying Wax NF, Stearic Acid, Hydroxyethylcellulose, Disodium EDTA, Sodium Metabisulfite, Fragrance, Diazolidinyl Urea, Methylparaben, Propylparaben, BHT, Tocopheryl (Vitamin E) Acetate, Beta-Carotene, Magnesium Ascorbyl Phosphate, Citric Acid.

Questions or Comments?

- Call toll-free:1-800-595-6230
- Visit us at www.porcelana.com